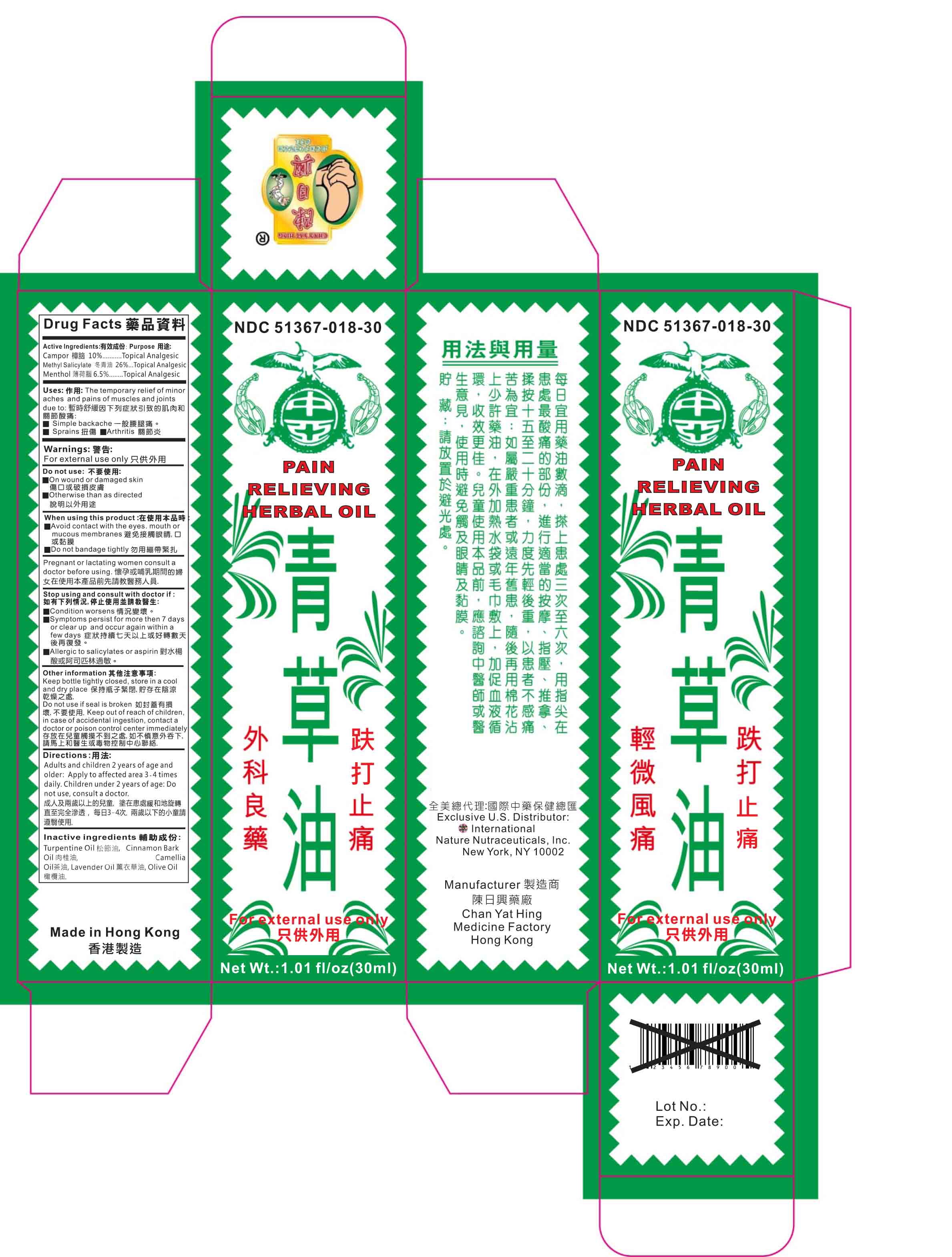 DRUG LABEL: Pain Reileving Herbal Oil
NDC: 51367-018 | Form: OIL
Manufacturer: International Nature Nutracetucals
Category: otc | Type: HUMAN OTC DRUG LABEL
Date: 20131020

ACTIVE INGREDIENTS: CAMPHOR (NATURAL) 2.99 1/1 1; METHYL SALICYLATE 9.16 1/1 1; MENTHOL 1.74 1/1 1
INACTIVE INGREDIENTS: TURPENTINE OIL; CINNAMON BARK OIL; CAMELLIA OIL; LAVENDER OIL; OLIVE OIL

Drug Facts

Active Ingredients:

Camphor- 10%

Methyl Salicylate- 26%

Menthol- 6.5%

Uses:

The temporary relief of minor

aches and pains of muscles and joints

due to: 暫時舒緩因下列症狀引致的肌肉和

Simple backache 一般腰腿痛。

Sprains 扭傷 Arthritis 關節炎

Warnings:

For external use only

Keep out of reach of Children

In case of ingestion, contact a doctor of poison control center immediately.

Stop Using and contact a doctor if:

Condition worsens 情況變壞。

Symptoms persist for more then 7 days

or clear up and occur again within a

few days 症狀持續七天以上或好轉數天

後再復發。

Allergic to salicylates or aspirin 對水楊

酸或阿司匹林過敏。

Other Information

Keep bottle tightly closed, store in a cool

and dry place 保持瓶子緊閉,貯存在陰涼

乾燥之處.

Do not use if seal is broken 如封蓋有損

壞,不要使用.

Do not use

On wound or damaged skin

傷口或破損皮膚

Otherwise than as directed

說明以外用途

Directions

Adults and children 2 years of age and

older: Apply to affected area 3-4 times

daily. Children under 2 years of age: Do

not use, consult a doctor.

成人及兩歲以上的兒童, 塗在患處緩和地旋轉

直至完全滲透， 每日3-4次. 兩歲以下的小童請

遵翳使用.

When using product

Avoid contact with the eyes. mouth or

mucous membranes 避免接觸眼睛,口

或黏膜

Do not bandage tightly 勿用繃帶緊扎

Pregnant or lactating women consult a

doctor before using. 懷孕或哺乳期間的婦

女在使用本產品前先請教醫務人員.

Inactive Ingredients

Turpentine Oil 松節油, Cinnamon Bark

Oil 肉桂油, Camellia

Oil茶油, Lavender Oil 薰衣草油, Olive Oil

橄欖油.